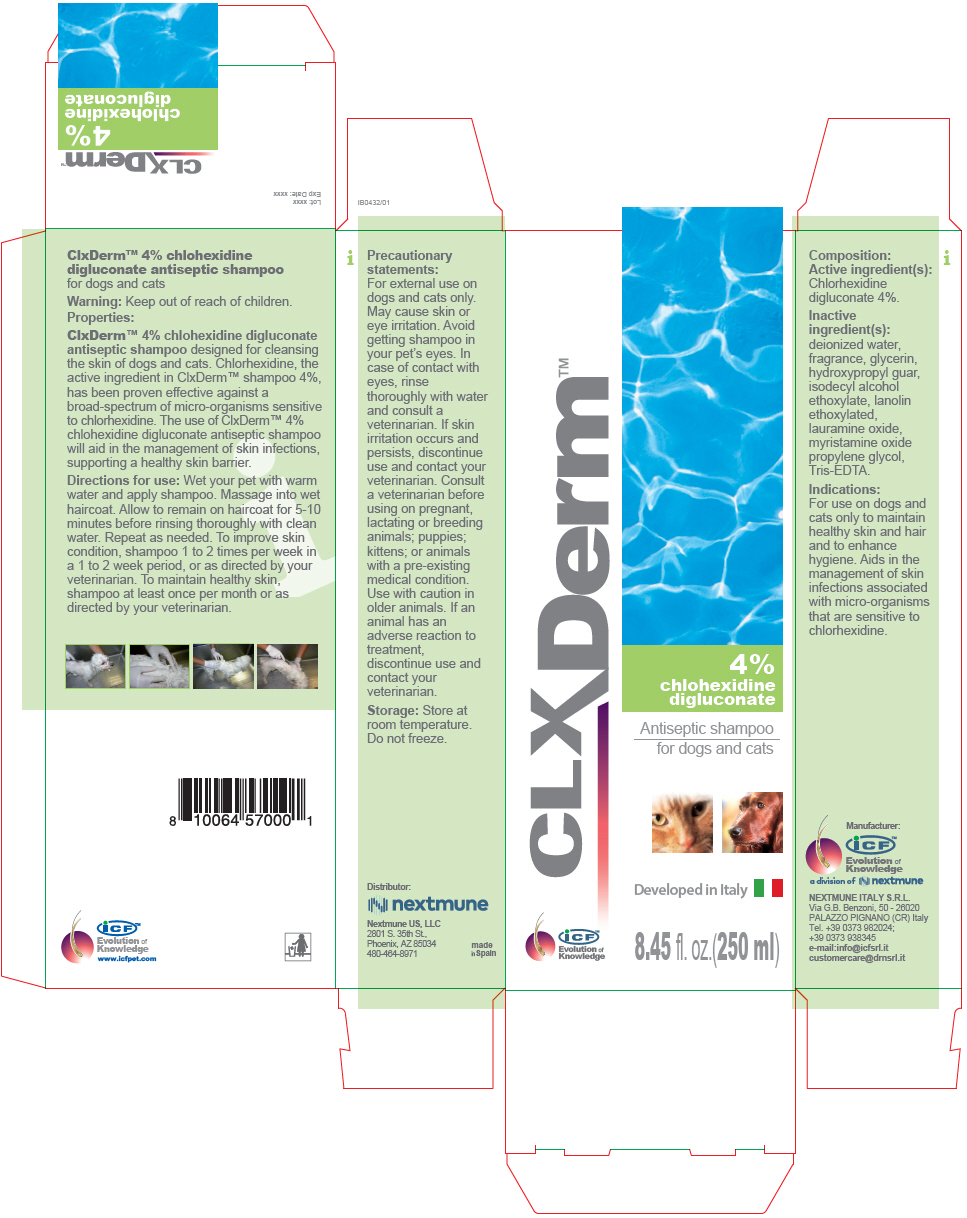 DRUG LABEL: Clx Derm
NDC: 86127-001 | Form: SHAMPOO
Manufacturer: Nextmune AB
Category: animal | Type: OTC ANIMAL DRUG LABEL
Date: 20220111

ACTIVE INGREDIENTS: CHLORHEXIDINE GLUCONATE 40 mg/1 mL
INACTIVE INGREDIENTS: water; glycerin; propylene glycol; GUARAPROLOSE (3500 MPA.S AT 1%); isodecyl alcohol; PEG-75 Lanolin; TROMETHAMINE; EDETATE SODIUM; MYRISTAMINE OXIDE; LAURAMINE OXIDE

CLXderm™

VETERINARY INDICATIONS

ClxDerm™ 4% chlohexidine
digluconate antiseptic shampoo
for dogs and cats

Warning: Keep out of reach of children.

Properties:

ClxDerm™ 4% chlohexidine digluconate antiseptic shampoo designed for cleansing the skin of dogs and cats. Chlorhexidine, the active ingredient in ClxDerm™ shampoo 4%, has been proven effective against a broad-spectrum of micro-organisms sensitive to chlorhexidine. The use of ClxDerm™ 4% chlohexidine digluconate antiseptic shampoo will aid in the management of skin infections, supporting a healthy skin barrier.

DOSAGE AND ADMINISTRATION

Directions for use: Wet your pet with warm water and apply shampoo. Massage into wet haircoat. Allow to remain on haircoat for 5-10 minutes before rinsing thoroughly with clean water. Repeat as needed. To improve skin condition, shampoo 1 to 2 times per week in a 1 to 2 week period, or as directed by your veterinarian. To maintain healthy skin, shampoo at least once per month or as directed by your veterinarian.

Precautionary statements:

For external use on dogs and cats only. May cause skin or eye irritation. Avoid getting shampoo in your pet's eyes. In case of contact with eyes, rinse thoroughly with water and consult a veterinarian. If skin irritation occurs and persists, discontinue use and contact your veterinarian. Consult a veterinarian before using on pregnant, lactating or breeding animals; puppies; kittens; or animals with a pre-existing medical condition. Use with caution in older animals. If an animal has an adverse reaction to treatment, discontinue use and contact your veterinarian.

Storage: Store at room temperature. Do not freeze.

Composition:

Active ingredient(s):

Chlorhexidine digluconate 4%.

Inactive ingredient(s): deionized water, fragrance, glycerin, hydroxypropyl guar, isodecyl alcohol ethoxylate, lanolin ethoxylated, lauramine oxide, myristamine oxide propylene glycol, Tris-EDTA.

Indications:

For use on dogs and cats only to maintain healthy skin and hair and to enhance hygiene. Aids in the management of skin infections associated with micro-organisms that are sensitive to chlorhexidine.

www.icfpet.com

Manufacturer:

iCF™
Evolution of
Knowledge

a division of nextmune

NEXTMUNE ITALY S.R.L.
Via G.B. Benzoni, 50 - 26020
PALAZZO PIGNANO (CR) Italy
Tel. +39 0373 982024;
+39 0373 938345
e-mail:info@icfsrl.it
customercare@drnsrl.it

Distributor:
Nextmune US, LLC
2801 S. 35th St.,
Phoenix, AZ 85034
480-464-8971

made
in Spain

PRINCIPAL DISPLAY PANEL - 250 ml Bottle Carton

CLXDerm™

4%
chlohexidine
digluconate

Antiseptic shampoo
for dogs and cats

Developed in Italy

iCF™
Evolution of
Knowledge

8.45 fl. oz.(250 ml)